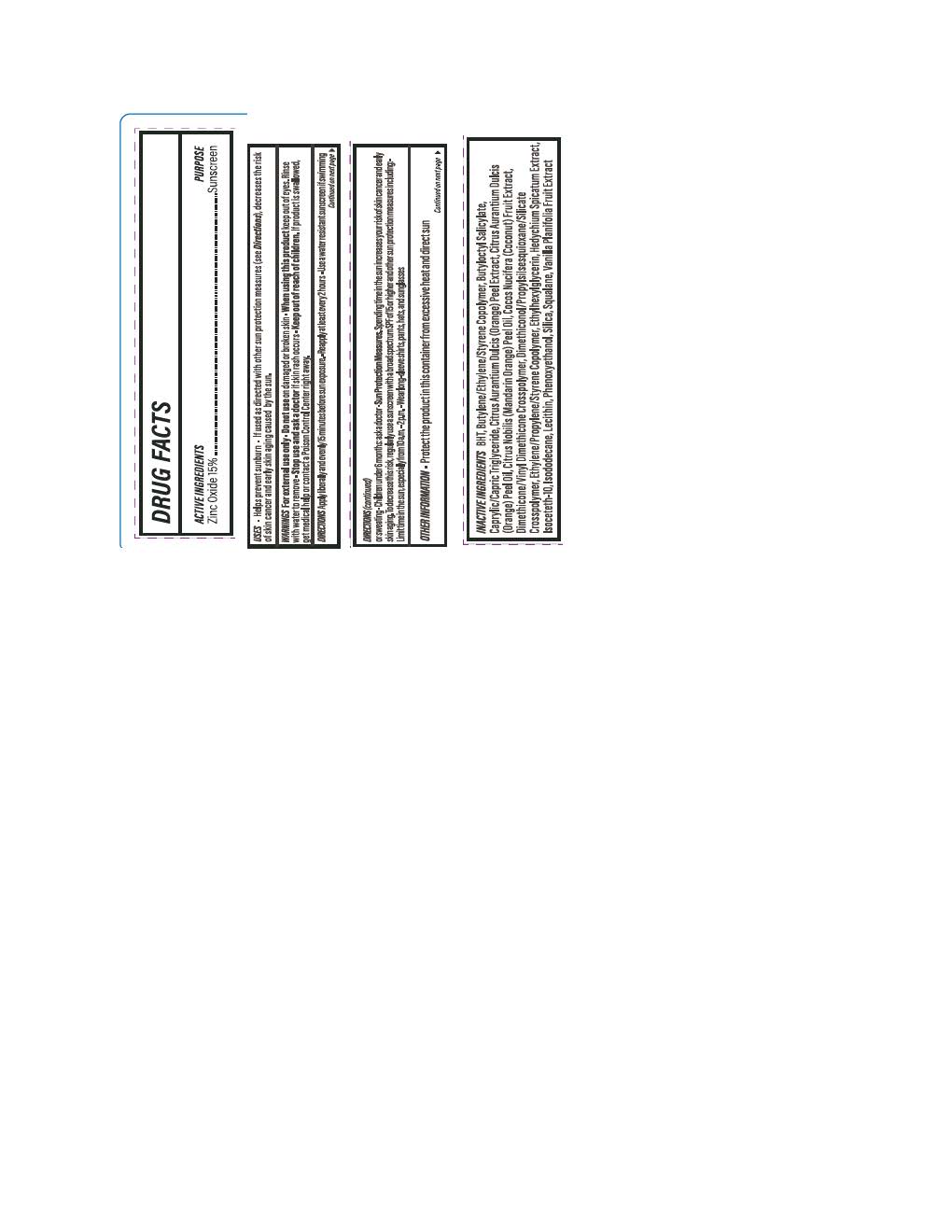 DRUG LABEL: Solarium Daily Essentials Skin Perfecting Primer
NDC: 84891-2188 | Form: LOTION
Manufacturer: Solarium Brands LLC
Category: otc | Type: HUMAN OTC DRUG LABEL
Date: 20251117

ACTIVE INGREDIENTS: ZINC OXIDE 165 mg/1 mL
INACTIVE INGREDIENTS: CITRUS AURANTIUM DULCIS (ORANGE) PEEL OIL; BHT; VANILLA PLANIFOLIA OIL; COCOS NUCIFERA (COCONUT) OIL; DIMETHICONE/VINYL DIMETHICONE CROSSPOLYMER (HARD PARTICLE); SILICON DIOXIDE; SQUALANE; ISODODECANE; PHENOXYETHANOL; HEDYCHIUM SPICATUM WHOLE; CITRUS AURANTIUM DULCIS (ORANGE) PEEL WAX; DIMETHICONOL/PROPYLSILSESQUIOXANE/SILICATE CROSSPOLYMER (450000000 MW); BUTYLOCTYL SALICYLATE; ISOCETETH-10; ETHYLHEXYLGLYCERIN; CITRUS NOBILIS (MANDARIN ORANGE) PEEL OIL; LECITHIN, SOYBEAN; CAPRYLIC/CAPRIC TRIGLYCERIDE

Solarium Daily Essentials Skin Perfecting Primer